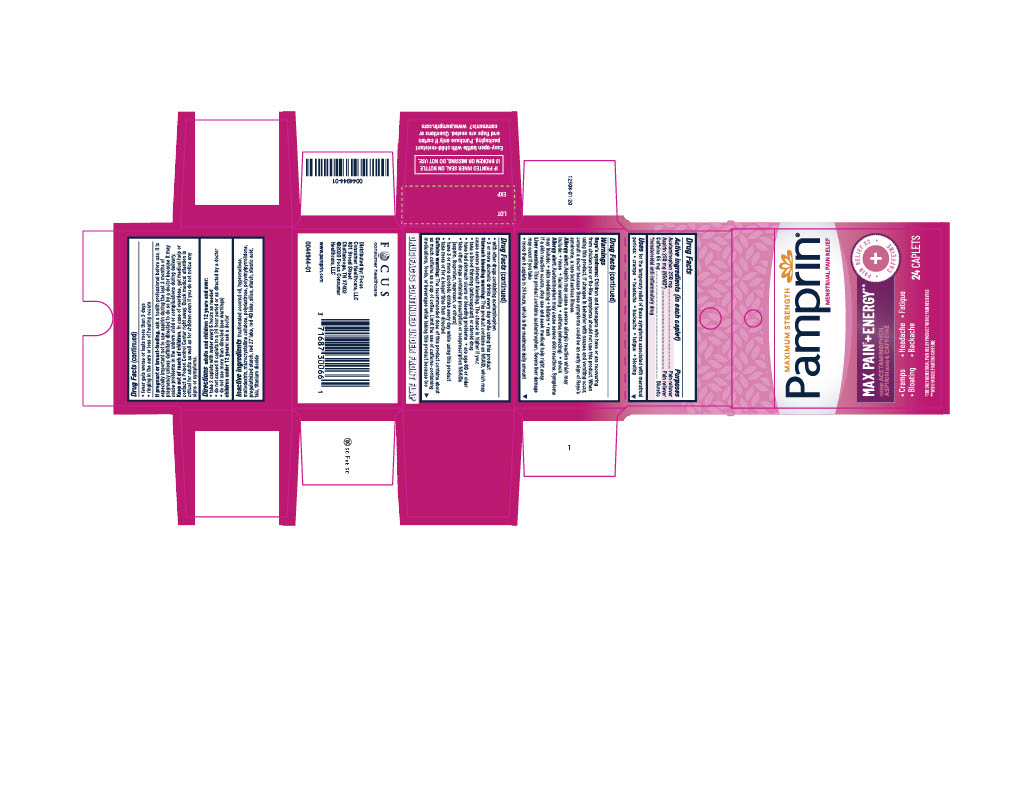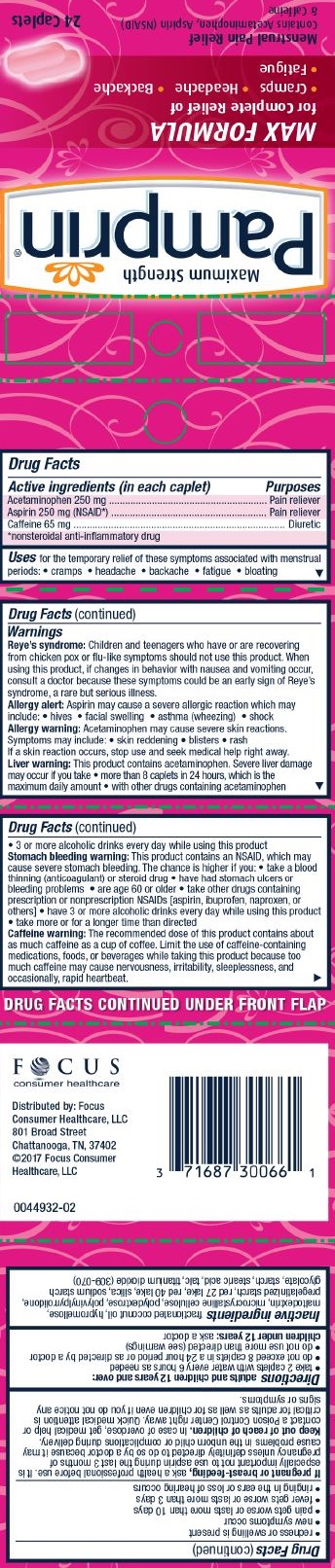 DRUG LABEL: Pamprin Max Menstrual Pain Relief
NDC: 71687-3006 | Form: TABLET, FILM COATED
Manufacturer: Focus Consumer Healthcare, LLC
Category: otc | Type: HUMAN OTC DRUG LABEL
Date: 20250414

ACTIVE INGREDIENTS: ACETAMINOPHEN 250 mg/1 1; ASPIRIN 250 mg/1 1; CAFFEINE 65 mg/1 1
INACTIVE INGREDIENTS: D&C RED NO. 27; FD&C RED NO. 40; MEDIUM-CHAIN TRIGLYCERIDES; HYPROMELLOSES; MALTODEXTRIN; CELLULOSE, MICROCRYSTALLINE; POLYDEXTROSE; SILICON DIOXIDE; STEARIC ACID; TALC; TITANIUM DIOXIDE; STARCH, CORN

Pamprin Max Menstrual Pain Relief

PURPOSE

Pain reliever

Diuretic

*nonsteroidal anti-inflammatory drug

ACTIVE INGREDIENT

(in each caplet)

Acetaminophen 250 mg

Aspirin 250 mg

Caffeine 65 mg

INACTIVE INGREDIENT

D&C Red No. 27 Lake, FD&C Red No. 40 Lake, fractionated coconut oil, hypromellose, maltodextrin, microcrystalline cellulose, polydextrose, polyvinylpyrrolidone, pregelatinized starch, silica, sodium starch glycolate, starch, stearic acid, talc, titanium dioxide (245-171)

INDICATIONS AND USAGE

For the temporary relief of these symptoms associated with menstrual periods:

- cramps
- headache
- backache
- fatigue
- bloating

WARNINGS

Reye’s syndrome: Children and teenagers who have or are recovering from chicken pox or flu-like symptoms should not use this product. When using this product, if changes in behavior with nausea and vomiting occur, consult a doctor because these symptoms could be an early sign of Reye’s syndrome, a rare but serious illness.

Allergy alert: Aspirin may cause a severe allergic reaction which may include:

- hives
- facial swelling
- asthma (wheezing)
- shock

Allergy warning: Acetaminophen may cause severe skin reactions. Symptoms may include:

- skin reddening
- blisters
- rash

If a skin reaction occurs, stop use and seek medical help right away.

Liver warning: This product contains acetaminophen. Severe liver damage may occur if you take

- more than 8 caplets in 24 hours, which is the maximum daily amount
- with other drugs containing acetaminophen
- 3 or more alcoholic drinks every day while using this product

Stomach bleeding warning: This product contains an NSAID, which may cause severe stomach bleeding. The chance is higher if you

- are age 60 or older
- have had stomach ulcers or bleeding problems
- take a blood thinning (anticoagulant) or steroid drug
- take other drugs containing prescription or nonprescription NSAIDs [aspirin, ibuprofen, naproxen, or others]
- have 3 or more alcoholic drinks every day while using this product
- take more or for a longer time than directed

Caffeine warning: The recommended dose of this product contains about as much caffeine as a cup of coffee. Limit the use of caffeine-containing medications, foods, or beverages while taking this product because too much caffeine may cause nervousness, irritability, sleeplessness, and occasionally, rapid heartbeat.

Do not use

• if you are allergic to aspirin or any other pain reliever/fever reducer

• with any other drug containing acetaminophen (prescription or nonprescription). If you are not sure whether a drug contains acetaminophen, ask a doctor or pharmacist.

Ask a doctor before use if

- you have liver disease
- the stomach bleeding warning applies to you
- you have a history of stomach problems, such as heartburn
- you have high blood pressure, heart disease, liver cirrhosis, or kidney disease
- you are taking a diuretic

Ask a doctor or pharmacist before use

if you are taking a prescription drug for gout, diabetes or arthritis

Stop use and ask a doctor if

- an allergic reaction occurs. Seek medical help right away.
- you experience any of the following signs of stomach bleeding:
  - feel faint
  - vomit blood
  - have bloody or black stools
  - have stomach pain that does not get better

- redness or swelling is present
- new symptoms occur
- pain gets worse or lasts more than 10 days
- fever gets worse or lasts more than 3 days
- ringing in the ears or loss of hearing occurs

If pregnant or breast-feeding,

ask a health professional before use. It is especially important not to use aspirin during the last 3 months of pregnancy unless definitely directed to do so by a doctor because it may cause problems in the unborn child or complications during delivery.

Keep out of reach of children.

In case of overdose, get medical help or contact a Poison Control Center right away. Quick medical attention is critical for adults as well as for children even if you do not notice any signs or symptoms.

When using this product

- you may get drowsy, avoid alcoholic beverages
- alcohol sedatives and tranquilizers may increase drowsiness
- use caution when driving or operating machinery
- excitability may occur especially in children

stop use and ask doctor if

- pain gets worse or lasts for more than 10 days
- fever gets worse or lasts for more than 3 days
- new symptoms occur
- redness or swelling is present

If pregnant or breastfeeding, ask a health professional before use.

Keep out of reach of children. In case of overdose, get medical help or contact a poison control center right away.

Keep out of reach of children. In case of overdose, get medical help or contact a poison control center right away.

DOSAGE AND ADMINISTRATION

Adults and children 12 years and over:

• take 2 caplets with water every 6 hours as needed

• do not exceed 8 caplets in a 24 hour period or as directed by a doctor

• do not use more than directed (see warnings)

children under 12 years: ask a doctor